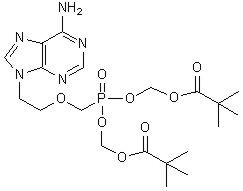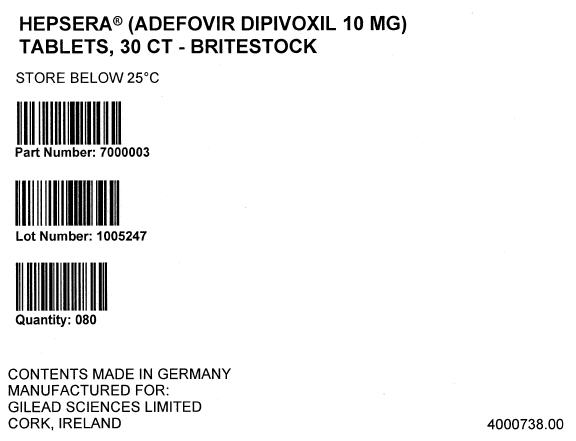 DRUG LABEL: Hepsera
NDC: 46014-0501 | Form: TABLET
Manufacturer: Excella GmbH
Category: prescription | Type: HUMAN PRESCRIPTION DRUG LABEL
Date: 20091027

ACTIVE INGREDIENTS: Adefovir Dipivoxil 10 mg/1 1

HIGHLIGHTS OF PRESCRIBING INFORMATION

These highlights do not include all the information needed to use HEPSERA safely and effectively. See full prescribing information for HEPSERA.
HEPSERA (adefovir dipivoxil) tablet for oral use
Initial U.S. Approval: 2002

WARNING: SEVERE ACUTE EXACERBATIONS OF HEPATITIS, NEPHROTOXICITY, HIV RESISTANCE, LACTIC ACIDOSIS AND SEVERE HEPATOMEGALY WITH STEATOSIS

See full prescribing information for complete boxed warning.

- Severe acute exacerbations of hepatitis may occur in patients who discontinue HEPSERA. Monitor hepatic function closely in these patients. (5.1)
- Chronic use of HEPSERA may result in nephrotoxicity in patients at risk of renal dysfunction or having underlying renal dysfunction. Monitor renal function closely in these patients. Dose adjustment may be required. (5.2)
- HIV resistance may emerge in chronic hepatitis B patients with unrecognized or untreated HIV infection. (5.3)
- Lactic acidosis and severe hepatomegaly with steatosis, including fatal cases, have been reported with the use of nucleoside analogues. (5.4)

RECENT MAJOR CHANGES

Warnings and Precautions
Nephrotoxicity (5.2) | 10/2009
Coadministration with Other Products (5.5) | 10/2009

1 INDICATIONS AND USAGE

HEPSERA is a nucleotide analogue indicated for the treatment of chronic hepatitis B in patients ≥12 years of age. (1)

2 DOSAGE AND ADMINISTRATION

- One tablet containing 10 mg adefovir dipivoxil once daily orally with or without food. (2.1)
- Dose adjustment in renal impairment for adults (2.2)

 | Creatinine Clearance (mL/min) [Creatinine clearance calculated by Cockcroft-Gault method using lean or ideal body weight.]
 | ≥50 | 30–49 | 10–29 | Hemodialysis Patients
Recommended dose and dosing interval | 10 mg every 24 hours | 10 mg every 48 hours | 10 mg every 72 hours | 10 mg every 7 days following dialysis

- No dose recommendations for (2.1):
  - Non-hemodialysis patients with creatinine clearance <10mL/min.
  - Adolescent patients with renal impairment.

3 DOSAGE FORMS AND STRENGTHS

Tablets: 10 mg (3)

4 CONTRAINDICATIONS

HEPSERA is contraindicated in patients with previously demonstrated hypersensitivity to any of the components of the product. (4)

5 WARNINGS AND PRECAUTIONS

- Severe acute exacerbations of hepatitis: Monitor hepatic function closely at repeated intervals for at least several months in patients who discontinue HEPSERA. (5.1)
- Nephrotoxicity: Monitor renal function during therapy for all patients, particularly those with pre-existing or other risks for renal impairment. Dose adjustment may be required. (5.2)
- HIV Resistance: Offer HIV testing to all patients prior to initiating HEPSERA. Untreated HIV may result in HIV resistance. (5.3)
- Lactic acidosis and severe hepatomegaly with steatosis: If suspected, suspend treatment. (5.4)
- Coadministration with Other Products: Do not administer HEPSERA concurrently with VIREAD or other tenofovir-containing products. (5.5)
- Clinical Resistance: For patients with lamivudine-resistant HBV use adefovir dipivoxil in combination with lamivudine. For all patients, consider modifying treatment in case serum HBV DNA remains above 1000 copies/mL with continued treatment. (5.6)

6 ADVERSE REACTIONS

Most common adverse reaction (>10%) in compensated disease patients is asthenia and in pre- and post-transplantation lamivudine-resistant liver disease patients is increased creatinine. (6)

To report SUSPECTED ADVERSE REACTIONS, contact Gilead at (1-800-GILEAD-5) or FDA at 1-800-FDA-1088 or www.fda.gov/medwatch

7 DRUG INTERACTIONS

- Co-administration with drugs that reduce renal function or compete for active tubular secretion may increase serum concentrations of adefovir or the co-administered drug. Monitor for HEPSERA associated adverse events. (7)

8 USE IN SPECIFIC POPULATIONS

- Pregnancy: No human data. Pregnancy registry available. (8.1)
- Nursing Mothers: Unknown if present in human milk (8.3)
- Pediatrics: Not recommended in children <12 years of age. (8.4, 2.1,14.4)
- Renal Impairment: Dose adjustment may be required. (2.2)

FULL PRESCRIBING INFORMATION

WARNING: SEVERE ACUTE EXACERBATIONS OF HEPATITIS, NEPHROTOXICITY, HIV RESISTANCE, LACTIC ACIDOSIS AND SEVERE HEPATOMEGALY WITH STEATOSIS

Severe acute exacerbations of hepatitis have been reported in patients who have discontinued anti-Hepatitis B therapy including HEPSERA. Hepatic function should be monitored closely with both clinical and laboratory follow-up for at least several months in patients who discontinue anti-Hepatitis B therapy. If appropriate, resumption of anti-Hepatitis B therapy may be warranted [see Warnings and Precautions (5.1)].

In patients at risk of or having underlying renal dysfunction, chronic administration of HEPSERA may result in nephrotoxicity. These patients should be monitored closely for renal function and may require dose adjustment [see Warnings and Precautions (5.2) and Dosage and Administration (2.2)].

HIV resistance may emerge in chronic hepatitis B patients with unrecognized or untreated Human Immunodeficiency Virus (HIV) infection treated with anti-hepatitis B therapies, such as therapy with HEPSERA, that may have activity against HIV [see Warnings and Precautions (5.3)].

Lactic acidosis and severe hepatomegaly with steatosis, including fatal cases, have been reported with the use of nucleoside analogs alone or in combination with other antiretrovirals [see Warnings and Precautions (5.4)].

1 INDICATIONS AND USAGE

HEPSERA is indicated for the treatment of chronic hepatitis B in patients 12 years of age and older with evidence of active viral replication and either evidence of persistent elevations in serum aminotransferases (ALT or AST) or histologically active disease.

This indication is based on histological, virological, biochemical, and serological responses in adult patients with HBeAg+ and HBeAg- chronic hepatitis B with compensated liver function, and with clinical evidence of lamivudine-resistant hepatitis B virus with either compensated or decompensated liver function.

For patients 12 to <18 years of age, the indication is based on virological and biochemical responses in patients with HBeAg+ chronic hepatitis B virus infection with compensated liver function.

2 DOSAGE AND ADMINISTRATION

2.1 Chronic Hepatitis B

The recommended dose of HEPSERA in chronic hepatitis B patients for patients ≥12 years of age with adequate renal function is 10 mg, once daily, taken orally, without regard to food. The optimal duration of treatment is unknown.

HEPSERA is not recommended for use in children less than 12 years of age.

2.2 Dose Adjustment in Renal Impairment

Significantly increased drug exposures were seen when HEPSERA was administered to adult patients with renal impairment [see Warnings and Precautions (5.2) and Clinical Pharmacology (12.3)]. Therefore, the dosing interval of HEPSERA should be adjusted in adult patients with baseline creatinine clearance <50 mL/min using the following suggested guidelines (see Table 1). The safety and effectiveness of these dosing interval adjustment guidelines have not been clinically evaluated.

Additionally, it is important to note that these guidelines were derived from data in patients with pre-existing renal impairment at baseline. They may not be appropriate for patients in whom renal insufficiency evolves during treatment with HEPSERA. Therefore, clinical response to treatment and renal function should be closely monitored in these patients.

Table 1. Dosing Interval Adjustment of HEPSERA in Adult Patients with Renal Impairment
 | Creatinine Clearance (mL/min) [Creatinine clearance calculated by Cockcroft-Gault method using lean or ideal body weight.]
 | ≥50 | 30–49 | 10–29 | Hemodialysis Patients
Recommended dose and dosing interval | 10 mg every 24 hours | 10 mg every 48 hours | 10 mg every 72 hours | 10 mg every 7 days following dialysis

The pharmacokinetics of adefovir have not been evaluated in non-hemodialysis patients with creatinine clearance <10 mL/min; therefore, no dosing recommendation is available for these patients.

No clinical data are available to make dosing recommendations in adolescent patients with renal insufficiency [see Warnings and Precautions (5.2)].

3 DOSAGE FORMS AND STRENGTHS

HEPSERA is available as tablets. Each tablet contains 10 mg of adefovir dipivoxil. The tablets are white and debossed with "10" and "GILEAD" on one side and the stylized figure of a liver on the other side.

4 CONTRAINDICATIONS

HEPSERA is contraindicated in patients with previously demonstrated hypersensitivity to any of the components of the product.

5 WARNINGS AND PRECAUTIONS

5.1 Exacerbation of Hepatitis after Discontinuation of Treatment

Severe acute exacerbation of hepatitis has been reported in patients who have discontinued anti-hepatitis B therapy, including therapy with HEPSERA. Hepatic function should be monitored at repeated intervals with both clinical and laboratory follow-up for at least several months in patients who discontinue HEPSERA. If appropriate, resumption of anti-hepatitis B therapy may be warranted.

In clinical trials of HEPSERA, exacerbations of hepatitis (ALT elevations 10 times the upper limit of normal or greater) occurred in up to 25% of patients after discontinuation of HEPSERA. These events were identified in studies GS-98-437 and GS-98-438 (N=492). Most of these events occurred within 12 weeks of drug discontinuation. These exacerbations generally occurred in the absence of HBeAg seroconversion, and presented as serum ALT elevations in addition to re-emergence of viral replication. In the HBeAg-positive and HBeAg-negative studies in patients with compensated liver function, the exacerbations were not generally accompanied by hepatic decompensation. However, patients with advanced liver disease or cirrhosis may be at higher risk for hepatic decompensation. Although most events appear to have been self-limited or resolved with re-initiation of treatment, severe hepatitis exacerbations, including fatalities, have been reported. Therefore, patients should be closely monitored after stopping treatment.

5.2 Nephrotoxicity

Nephrotoxicity characterized by a delayed onset of gradual increases in serum creatinine and decreases in serum phosphorus was historically shown to be the treatment-limiting toxicity of adefovir dipivoxil therapy at substantially higher doses in HIV-infected patients (60 and 120 mg daily) and in chronic hepatitis B patients (30 mg daily). Chronic administration of HEPSERA (10 mg once daily) may result in delayed nephrotoxicity. The overall risk of nephrotoxicity in patients with adequate renal function is low. However, this is of special importance in patients at risk of or having underlying renal dysfunction and patients taking concomitant nephrotoxic agents such as cyclosporine, tacrolimus, aminoglycosides, vancomycin and non-steroidal anti-inflammatory drugs [see Adverse Reactions (6.2) and Clinical Pharmacology (12.3)]. It is recommended that creatinine clearance is calculated in all patients prior to initiating therapy with HEPSERA.

It is important to monitor renal function for all patients during treatment with HEPSERA, particularly for those with pre-existing or other risks for renal impairment. Patients with renal insufficiency at baseline or during treatment may require dose adjustment [see Dosage and Administration (2.2)]. The risks and benefits of HEPSERA treatment should be carefully evaluated prior to discontinuing HEPSERA in a patient with treatment-emergent nephrotoxicity.

Pediatric Patients

The efficacy and safety of HEPSERA have not been studied in patients less than 18 years of age with different degrees of renal impairment and no data are available to make dosage recommendations in these patients [see Dosage and Administration (2.2)]. Caution should be exercised when prescribing HEPSERA to adolescents with underlying renal dysfunction, and renal function in these patients should be closely monitored.

5.3 HIV Resistance

Prior to initiating HEPSERA therapy, HIV antibody testing should be offered to all patients. Treatment with anti-hepatitis B therapies, such as HEPSERA, that have activity against HIV in a chronic hepatitis B patient with unrecognized or untreated HIV infection may result in emergence of HIV resistance. HEPSERA has not been shown to suppress HIV RNA in patients; however, there are limited data on the use of HEPSERA to treat patients with chronic hepatitis B co-infected with HIV.

5.4 Lactic Acidosis/Severe Hepatomegaly with Steatosis

Lactic acidosis and severe hepatomegaly with steatosis, including fatal cases, have been reported with the use of nucleoside analogs alone or in combination with antiretrovirals.

A majority of these cases have been in women. Obesity and prolonged nucleoside exposure may be risk factors. Particular caution should be exercised when administering nucleoside analogs to any patient with known risk factors for liver disease; however, cases have also been reported in patients with no known risk factors. Treatment with HEPSERA should be suspended in any patient who develops clinical or laboratory findings suggestive of lactic acidosis or pronounced hepatotoxicity (which may include hepatomegaly and steatosis even in the absence of marked transaminase elevations).

5.5 Coadministration with Other Products

HEPSERA should not be used concurrently with VIREAD (tenofovir disoproxil fumarate) or tenofovir disoproxil fumarate-containing products including TRUVADA (emtricitabine/tenofovir disoproxil fumarate combination tablet) and ATRIPLA (efavirenz/emtricitabine/tenofivir disoproxil fumarate combination tablet).

5.6 Clinical Resistance

Resistance to adefovir dipivoxil can result in viral load rebound which may result in exacerbation of hepatitis B and, in the setting of diminished hepatic function, lead to liver decompensation and possible fatal outcome.

In order to reduce the risk of resistance in patients with lamivudine resistant HBV, adefovir dipivoxil should be used in combination with lamivudine and not as adefovir dipivoxil monotherapy.

In order to reduce the risk of resistance in all patients receiving adefovir dipivoxil monotherapy, a modification of treatment should be considered if serum HBV DNA remains above 1000 copies/mL with continued treatment.

Long-term (144 week) data from Study 438 (n=124) show that patients with HBV DNA levels greater than 1000 copies/mL at Week 48 of treatment with HEPSERA were at greater risk of developing resistance than patients with serum HBV DNA levels below 1000 copies/mL at Week 48 of therapy.

6 ADVERSE REACTIONS

The following adverse reactions are discussed in other sections of the labeling:

- Severe acute exacerbations of Hepatitis [see Boxed Warning, Warnings and Precautions (5.1)]
- Nephrotoxicity [see Boxed Warning , Warnings and Precautions (5.2)]

6.1 Clinical Trials Experience

Because clinical trials are conducted under widely varying conditions, adverse reaction rates observed in the clinical trials of a drug cannot be directly compared to rates in the clinical trials of another drug and may not reflect the rates observed in practice.

Clinical and laboratory evidence of exacerbations of hepatitis have occurred after discontinuation of treatment with HEPSERA.

Adverse reactions to HEPSERA identified from placebo-controlled and open label studies include the following: asthenia, headache, abdominal pain, diarrhea, nausea, dyspepsia, flatulence, increased creatinine, and hypophosphatemia.

The incidence of these adverse reactions in studies 437 and 438, where 522 patients with chronic hepatitis B and compensated liver disease received double-blind treatment with HEPSERA (n=294) or placebo (n=228) for 48 weeks is presented in Table 2. Patients who received open-label HEPSERA for up to 240 weeks in Study 438 reported adverse reactions similar in nature and severity to those reported in the first 48 weeks.

Table 2 Adverse Reactions (Grades 1–4) Reported in ≥3% of All HEPSERA-Treated Patients in Pooled Studies 437–438 Studies (0–48 Weeks) [In these studies, the overall incidence of adverse reactions with HEPSERA was similar to that reported with placebo. The incidence of adverse reactions is derived from treatment-related events as identified by the study investigators.]
Adverse Reaction | HEPSERA 10mg (N=294) | Placebo (N=228)
Asthenia | 13% | 14%
Headache | 9% | 10%
Abdominal Pain | 9% | 11%
Nausea | 5% | 8%
Flatulence | 4% | 4%
Diarrhea | 3% | 4%
Dyspepsia | 3% | 2%

No patients treated with HEPSERA developed a confirmed serum creatinine increase ≥0.5 mg/dL or confirmed phosphorus decrease ≤2 mg/dL from baseline by Week 48. By Week 96, 2% of HEPSERA-treated patients, by Kaplan-Meier estimate, had increases in serum creatinine ≥0.5 mg/dL from baseline (no placebo-controlled results were available for comparison beyond Week 48). For patients who chose to continue HEPSERA for up to 240 weeks in Study 438, 4 of 125 patients (3%) had a confirmed increase of 0.5 mg/dL from baseline. The creatinine elevation resolved in 1 patient who permanently discontinued treatment and remained stable in 3 patients who continued treatment. For 65 patients who chose to continue HEPSERA for up to 240 weeks in Study 437, 6 had a confirmed increase in serum creatinine of ≥0.5 mg/dL from baseline with 2 patients discontinuing from the study due to the elevated serum creatinine concentration. See Adverse Reactions (6.2) for changes in serum creatinine in patients with underlying renal insufficiency at baseline.

6.2 Special Risk Patients

Pre- and Post-Liver Transplantation Patients

Additional adverse reactions observed from an open-label study (Study 435) in pre- and post- liver transplantation patients with chronic hepatitis B and lamivudine-resistant hepatitis B administered HEPSERA once daily for up to 203 weeks include: abnormal renal function, renal failure, vomiting, rash, and pruritus.

Changes in renal function occurred in pre-and post-liver transplantation patients with risk factors for renal dysfunction, including concomitant use of cyclosporine and tacrolimus, renal insufficiency at baseline, hypertension, diabetes, and on-study transplantation. Therefore, the contributory role of HEPSERA to these changes in renal function is difficult to assess.

Increases in serum creatinine ≥0.3 mg/dL from baseline were observed in 37% and 53% of pre-liver transplantation patients by Weeks 48 and 96, respectively, by Kaplan-Meier estimates. Increases in serum creatinine ≥0.3 mg/dL from baseline were observed in 32% and 51% of post-liver transplantation patients by Weeks 48 and 96, respectively, by Kaplan-Meier estimates. Serum phosphorus values <2 mg/dL were observed in 3/226 (1.3%) of pre-liver transplantation patients and in 6/241 (2.5%) of post-liver transplantation patients by last study visit. Four percent (19 of 467) of patients discontinued treatment with HEPSERA due to renal adverse events.

6.3 Pediatric Patients

Assessment of adverse reactions is based on a placebo-controlled study (Study 518) in which 173 pediatric patients aged 2 to <18 years with chronic hepatitis B and compensated liver disease received double-blind treatment with HEPSERA (n=115), or placebo (n=58) for 48 weeks [see Clinical Studies (14.4) and Use In Specific Populations (8.4)].

The safety profile of HEPSERA in patients ≥12 to <18 years of age (n=56) was similar to that observed in adults. No pediatric patients treated with HEPSERA developed a confirmed serum creatinine increase ≥ 0.5 mg/dL or confirmed phosphorus decrease to <2 mg/dL from baseline by Week 48.

6.4 Post-Marketing Experience

In addition to adverse reaction reports from clinical trials, the following possible adverse reactions have also been identified during post-approval use of adefovir dipivoxil. Because these events have been reported voluntarily from a population of unknown size, estimates of frequency cannot be made.

Metabolism and Nutrition Disorders: hypophosphatemia

Gastrointestinal Disorders: pancreatitis

Musculoskeletal System and Connective Tissue Disorders: myopathy, osteomalacia (both associated with proximal renal tubulopathy)

Renal and Urinary Disorders: renal failure, Fanconi syndrome, proximal renal tubulopathy

7 DRUG INTERACTIONS

Since adefovir is eliminated by the kidney, co-administration of HEPSERA with drugs that reduce renal function or compete for active tubular secretion may increase serum concentrations of either adefovir and/or these co-administered drugs [see Clinical Pharmacology (12.3)].

Patients should be monitored closely for adverse events when HEPSERA is co-administered with drugs that are excreted renally or with other drugs known to affect renal function [see Warnings and Precautions (5.2)].

HEPSERA should not be administered in combination with VIREAD [see Warnings and Precautions (5.5)].

8 USE IN SPECIFIC POPULATIONS

8.1 Pregnancy

Teratogenic Effects: Pregnancy Category C

There are no adequate and well-controlled studies of HEPSERA in pregnant women. Chronic hepatitis B is a serious condition that requires treatment. HEPSERA should be used during pregnancy only if the potential benefit to the mother justifies the potential risk to the fetus.

Reproduction studies with oral administration of adefovir dipivoxil to pregnant rats and rabbits showed no evidence of embryotoxicity or teratogenicity at systemic exposures equivalent to 23 times (rats) and 40 times (rabbits) that achieved in humans at the therapeutic dose. However, embryotoxicity and an increased incidence of fetal malformations (anasarca, depressed eye bulge, umbilical hernia and kinked tail) occurred when adefovir was administered intravenously to pregnant rats at 38 times the human therapeutic exposure. These adverse reproductive effects did not occur following an intravenous dose where exposure was 12 times the human therapeutic exposure.

Because animal reproduction studies are not always predictive of human response, HEPSERA should be used during pregnancy only if clearly needed and after careful consideration of the risks and benefits [see Nonclinical Toxicology (13.2)].

Pregnancy Registry

To monitor fetal outcomes of pregnant women exposed to HEPSERA, a pregnancy registry has been established. Healthcare providers are encouraged to register patients by calling 1-800-258-4263.

8.2 Labor and Delivery

There are no studies in pregnant women and no data on the effect of HEPSERA on transmission of HBV from mother to infant. Therefore, appropriate infant immunizations should be used to prevent neonatal acquisition of hepatitis B virus.

8.3 Nursing Mothers

It is not known whether adefovir is excreted in human milk.

Because many drugs are excreted into human milk and because of the potential for serious adverse reactions in nursing infants from HEPSERA, a decision should be made whether to discontinue nursing or to discontinue drug, taking into account the importance of the drug to the mother.

8.4 Pediatric Use

Pediatric patients 12 to <18 years: The safety, efficacy, and pharmacokinetics of HEPSERA in pediatric patients (aged ≥12 to <18 years) were evaluated in a double-blind, randomized, placebo-controlled study (GS-US-103-518, Study 518) in 83 pediatric patients with chronic hepatitis B and compensated liver disease. The proportion of patients treated with HEPSERA who achieved the primary efficacy endpoint of serum HBV DNA <1,000 copies/mL and normal ALT levels at the end of 48 weeks blinded treatment was significantly greater (23%) when compared to placebo-treated patients (0%). [see Clinical Studies (14.4), Dosage And Administration (2) and Adverse Reactions (6.3)].

Pediatric patients 2 to <12 years: Patients 2 to <12 years of age were also evaluated in Study 518. The efficacy of adefovir dipivoxil was not significantly different from placebo in patients less than 12 years of age.

Hepsera is not recommended for use in children below 12 years of age.

8.5 Geriatric Use

Clinical studies of HEPSERA did not include sufficient numbers of patients aged 65 and over to determine whether they respond differently from younger patients. In general, caution should be exercised when prescribing to elderly patients since they have greater frequency of decreased renal or cardiac function due to concomitant disease or other drug therapy.

8.6 Patients with Impaired Renal Function

It is recommended that the dosing interval for HEPSERA be modified in adult patients with baseline creatinine clearance <50 mL/min. The pharmacokinetics of adefovir have not been evaluated in non-hemodialysis patients with creatinine clearance <10 mL/min or in adolescent patients with renal insufficiency; therefore, no dosing recommendations are available for these patients. [see Dosage And Administration (2.2) and Warning And Precautions (5.2)].

10 OVERDOSAGE

Doses of adefovir dipivoxil 500 mg daily for 2 weeks and 250 mg daily for 12 weeks have been associated with gastrointestinal side effects. If overdose occurs the patient must be monitored for evidence of toxicity, and standard supportive treatment applied as necessary.

Following a 10 mg single dose of HEPSERA, a four-hour hemodialysis session removed approximately 35% of the adefovir dose.

11 DESCRIPTION

HEPSERA® is the tradename for adefovir dipivoxil, a diester prodrug of adefovir. Adefovir is an acyclic nucleotide analog with activity against human hepatitis B virus (HBV).

The chemical name of adefovir dipivoxil is 9-[2-[[bis[(pivaloyloxy)methoxy]-phosphinyl]-methoxy]ethyl]adenine. It has a molecular formula of C20H32N5O8P, a molecular weight of 501.48 and the following structural formula:

Adefovir dipivoxil is a white to off-white crystalline powder with an aqueous solubility of 19 mg/mL at pH 2.0 and 0.4 mg/mL at pH 7.2. It has an octanol/aqueous phosphate buffer (pH 7) partition coefficient (log p) of 1.91.

HEPSERA tablets are for oral administration. Each tablet contains 10 mg of adefovir dipivoxil and the following inactive ingredients: croscarmellose sodium, lactose monohydrate, magnesium stearate, pregelatinized starch, and talc.

12 CLINICAL PHARMACOLOGY

12.1 Mechanism of Action

Adefovir is an antiviral drug. [see Clinical Pharmacology (12.4)].

12.3 Pharmacokinetics

Adult Subjects

The pharmacokinetics of adefovir have been evaluated in healthy volunteers and patients with chronic hepatitis B. Adefovir pharmacokinetics are similar between these populations.

Absorption

Adefovir dipivoxil is a diester prodrug of the active moiety adefovir. Based on a cross study comparison, the approximate oral bioavailability of adefovir from HEPSERA is 59%.

Following oral administration of a 10 mg single dose of HEPSERA to chronic hepatitis B patients (N=14), the peak adefovir plasma concentration (Cmax) was 18.4 ± 6.26 ng/mL (mean ± SD) and occurred between 0.58 and 4.00 hours (median=1.75 hours) post dose. The adefovir area under the plasma concentration-time curve (AUC0–∞) was 220 ± 70.0 ng∙h/mL. Plasma adefovir concentrations declined in a biexponential manner with a terminal elimination half-life of 7.48 ± 1.65 hours.

The pharmacokinetics of adefovir in subjects with adequate renal function were not affected by once daily dosing of 10 mg HEPSERA over seven days. The impact of long-term once daily administration of 10 mg HEPSERA on adefovir pharmacokinetics has not been evaluated.

Effects of Food on Oral Absorption

Adefovir exposure was unaffected when a 10 mg single dose of HEPSERA was administered with food (an approximately 1000 kcal high-fat meal). HEPSERA may be taken without regard to food.

Distribution

In vitro binding of adefovir to human plasma or human serum proteins is ≤4% over the adefovir concentration range of 0.1 to 25 µg/mL. The volume of distribution at steady-state following intravenous administration of 1.0 or 3.0 mg/kg/day is 392 ± 75 and 352 ± 9 mL/kg, respectively.

Metabolism and Elimination

Following oral administration, adefovir dipivoxil is rapidly converted to adefovir. Forty-five percent of the dose is recovered as adefovir in the urine over 24 hours at steady state following 10 mg oral doses of HEPSERA. Adefovir is renally excreted by a combination of glomerular filtration and active tubular secretion [see Drug Interactions (7) and Clinical Pharmacology (12.3)].

Assessment of Drug Interactions

Adefovir dipivoxil is rapidly converted to adefovir in vivo. At concentrations substantially higher (>4000-fold) than those observed in vivo, adefovir did not inhibit any of the common human CYP450 enzymes, CYP1A2, CYP2C9, CYP2C19, CYP2D6, and CYP3A4. Adefovir is not a substrate for these enzymes. However, the potential for adefovir to induce CYP450 enzymes is unknown. Based on the results of these in vitro experiments and the renal elimination pathway of adefovir, the potential for CYP450 mediated interactions involving adefovir as an inhibitor or substrate with other medicinal products is low.

The pharmacokinetics of adefovir have been evaluated in healthy adult volunteers following multiple dose administration of HEPSERA (10 mg once daily) in combination with lamivudine (100 mg once daily) (N=18), trimethoprim/sulfamethoxazole (160/800 mg twice daily) (N=18), acetaminophen (1000 mg four times daily) (N=20), ibuprofen (800 mg three times daily) (N=18), and enteric coated didanosine (400 mg) (N=21). The pharmacokinetics of adefovir have also been evaluated in post-liver transplantation patients following multiple dose administration of HEPSERA (10 mg once daily) in combination with tacrolimus (N=16). The pharmacokinetics of adefovir have been evaluated in healthy volunteers following single dose pegylated interferon α-2a (PEG-IFN) (180 µg) (N=15).

Adefovir did not alter the pharmacokinetics of lamivudine, trimethoprim/sulfamethoxazole, acetaminophen, ibuprofen, enteric coated didanosine (didanosine EC), or tacrolimus. The evaluation of the effect of adefovir on the pharmacokinetics of pegylated interferon α-2a was inconclusive due to the high variability of pegylated interferon alpha-2a.

The pharmacokinetics of adefovir were unchanged when HEPSERA was coadministered with lamivudine, trimethoprim/sulfamethoxazole, acetaminophen, didanosine EC, tacrolimus (based on cross study comparison), and pegylated interferon α-2a. When HEPSERA was coadministered with ibuprofen (800 mg three times daily) increases in adefovir Cmax (33%), AUC (23%) and urinary recovery were observed. This increase appears to be due to higher oral bioavailability, not a reduction in renal clearance of adefovir.

Apart from lamivudine, trimethoprim/sulfamethoxazole, and acetaminophen, the effects of co-administration of HEPSERA with drugs that are excreted renally, or other drugs known to affect renal function have not been evaluated.

The effect of adefovir on cyclosporine concentrations is not known.

No drug interaction studies have been performed in adolescent patients aged ≥12 years to <18 years.

Special Populations

Gender

The pharmacokinetics of adefovir were similar in male and female patients.

Race

The pharmacokinetics of adefovir have been shown to be comparable in Caucasians and Asians. Pharmacokinetic data are not available for other racial groups.

Geriatric Patients

Pharmacokinetic studies have not been conducted in the elderly.

Pediatric Patients

The pharmacokinetics of adefovir were assessed from drug plasma concentrations in 53 HBeAg positive hepatitis B pediatric patients with compensated liver disease. The exposure of adefovir following a 48 week daily treatment with adefovir dipivoxil 10 mg tablet in pediatric patients aged ≥ 12 to <18 years (Cmax = 23.3 ng/ml and AUC0–24 = 248.8 ng∙h/ml) was comparable to that observed in adult patients.

Renal Impairment

In adults with moderately or severely impaired renal function or with end-stage renal disease (ESRD) requiring hemodialysis, Cmax, AUC, and half-life (T1/2) were increased compared to adults with normal renal function. It is recommended that the dosing interval of HEPSERA be modified in these patients [see Dosage and Administration (2.2)].

The pharmacokinetics of adefovir in non-chronic hepatitis B patients with varying degrees of renal impairment are described in Table 3. In this study, subjects received a 10 mg single dose of HEPSERA.

Table 3. Pharmacokinetic Parameters (Mean ± SD) of Adefovir in Patients with Varying Degrees of Renal Function
Renal Function Group | Unimpaired | Mild | Moderate | Severe
Baseline creatinine clearance (mL/min) | >80 (N=7) | 50–80 (N=8) | 30–49 (N=7) | 10–29 (N=10)
Cmax (ng/mL) | 17.8 ± 3.22 | 22.4 ± 4.04 | 28.5 ± 8.57 | 51.6 ± 10.3
AUC 0–∞ (ng∙h/mL) | 201 ± 40.8 | 266 ± 55.7 | 455 ± 176 | 1240 ± 629
CL/F (mL/min) | 469 ± 99.0 | 356 ± 85.6 | 237 ± 118 | 91.7 ± 51.3
CLrenal (mL/min) | 231 ± 48.9 | 148 ± 39.3 | 83.9 ± 27.5 | 37.0 ± 18.4

A four-hour period of hemodialysis removed approximately 35% of the adefovir dose. The effect of peritoneal dialysis on adefovir removal has not been evaluated.

The pharmacokinetics of adefovir have not been studied in adolescent patients with renal dysfunction [see Use in Specific Populations (8.4)].

Hepatic Impairment

The pharmacokinetics of adefovir following a 10 mg single dose of HEPSERA have been studied in non-chronic hepatitis B patients with hepatic impairment. There were no substantial alterations in adefovir pharmacokinetics in patients with moderate and severe hepatic impairment compared to unimpaired patients. No change in HEPSERA dosing is required in patients with hepatic impairment.

12.4 Microbiology

Mechanism of Action

Adefovir is an acyclic nucleotide analog of adenosine monophosphate which is phosphorylated to the active metabolite adefovir diphosphate by cellular kinases. Adefovir diphosphate inhibits HBV DNA polymerase (reverse transcriptase) by competing with the natural substrate deoxyadenosine triphosphate and by causing DNA chain termination after its incorporation into viral DNA. The inhibition constant (Ki) for adefovir diphosphate for HBV DNA polymerase was 0.1 µM. Adefovir diphosphate is a weak inhibitor of human DNA polymerases α and γ with Ki values of 1.18 µM and 0.97 µM, respectively.

Antiviral Activity

The concentration of adefovir that inhibited 50% of viral DNA synthesis (EC50) in HBV transfected human hepatoma cell lines ranged from 0.2 to 2.5 µM. The combination of adefovir with lamivudine showed additive anti-HBV activity.

Resistance

Clinical isolates with genotypic changes conferring reduced susceptibility in cell culture to nucleoside analog reverse transcriptase inhibitors for the treatment of HBV infection have been observed. Long-term resistance analyses performed by genotyping samples from all adefovir dipivoxil-treated patients with detectable serum HBV DNA demonstrated that amino acid substitutions rtN236T and rtA181T/V have been observed in association with adefovir resistance. In cell culture, the rtN236T substitution demonstrated 4- to 14-fold, the rtA181V substitution 2.5- to 4.2-fold, and the rtA181T substitution 1.3- to 1.9-fold reduced susceptibility to adefovir.

In HBeAg-positive nucleoside-naïve patient isolates (Study GS-98-437, N=171), no adefovir resistance-associated substitutions were observed at Week 48. Sixty-five patients continued on long term treatment after a median duration on adefovir dipivoxil of 235 weeks (range 110–279 weeks). Isolates from 16 of 38 (42%) patients developed adefovir resistance-associated substitutions in the setting of virologic failure (confirmed increase of ≥1 log10 HBV DNA copies/mL above nadir or never suppressed below 10^3 copies/mL). The substitutions included rtN236T (n=2), rtA181V (n=4), rtA181T (n=3), rtA181T+rtN236T (n=5), and rtA181V+rtN236T (n=2). In HBeAg-negative nucleoside-naïve patients (Study GS-98-438), isolates from 30 patients were identified with adefovir resistance-associated substitutions with a cumulative probability of 0%, 3%, 11%, 19%, and 30% at 48, 96, 144, 192, and 240 weeks, respectively. Of those 30 patients, 22 had a confirmed increase of ≥1 log10 HBV DNA copies/mL above nadir or never achieved HBV DNA levels below 10^3 copies/mL; an additional 8 patients had adefovir resistance-associated substitutions without virologic failure. In addition, the long term (4 to 5 years) development of resistance to adefovir dipivoxil was significantly lower in patients who had serum HBV DNA below the limit of quantification (less than 1,000 copies/mL) at Week 48 as compared to patients who had serum HBV DNA above 1,000 copies/mL at Week 48.

In an open-label study of pre- and post-liver transplantation patients (Study GS-98-435), isolates from 129 patients with clinical evidence of lamivudine-resistant hepatitis B virus at baseline were evaluated for adefovir resistance-associated substitutions. The incidence of adefovir resistance-associated (rtN236T or rtA181T/V) substitutions was 0% at 48 weeks. Isolates from four patients developed the rtN236T substitution after 72 weeks of adefovir dipivoxil therapy. Development of the rtN236T substitution was associated with serum HBV DNA rebound. All 4 patients who developed the rtN236T substitution in their HBV had discontinued lamivudine therapy before the development of genotypic resistance and all 4 lost the lamivudine resistance-associated substitutions present at baseline. In a study of 35 HIV/HBV co-infected patients with lamivudine-resistant HBV (Study 460i) who added adefovir dipivoxil to lamivudine, no adefovir resistance-associated substitutions were observed in HBV isolates from 15/35 patients tested up to 144 weeks of therapy.

Clinical resistance in pediatric patients

In a Phase 3 pediatric Study GS-US-103-518, HBV isolates from 49 of 56 pediatric subjects (aged 12 to 17 years) had serum HBV DNA >169 copies/mL and were evaluated for adefovir resistance-associated substitutions. rtN236T and/or rtA181V adefovir resistance-associated substitutions were not observed at Week 48. However, the rtA181T substitution was present in baseline and Week 48 isolates from 2 pediatric patients.

Cross-resistance

Recombinant HBV variants containing lamivudine-resistance-associated substitutions (rtL180M, rtM204I, rtM204V, rtL180M + rtM204V, rtV173L + rtL180M + rtM204V) were susceptible to adefovir in cell culture. Adefovir dipivoxil has also demonstrated anti-HBV activity (median reduction in serum HBV DNA of 4.1 log10 copies/mL) in patients with HBV containing lamivudine-resistance-associated substitutions (Study 435). Adefovir also demonstrated in cell culture activity against HBV variants with entecavir resistance-associated substitutions (rtT184G, rtS202I, rtM250V). HBV variants with DNA polymerase substitutions rtT128N and rtR153Q or rtW153Q associated with resistance to hepatitis B virus immunoglobulin were susceptible to adefovir in cell culture.

HBV variants expressing the adefovir resistance-associated substitution rtN236T showed no change in susceptibility to entecavir in cell culture, and a 2- to 3-fold decrease in lamivudine susceptibility. HBV mutants with the adefovir resistance-associated substitution rtA181V showed a range of decreased susceptibilities to lamivudine of 1- to 14-fold and a 12-fold decrease in susceptibility to entecavir. In patients whose HBV expressed the rtA181V substitution (n=2) or the rtN236T substitution (n=3), a reduction in serum HBV DNA of 2.4 to 3.1 and 2.0 to 5.1 log10 copies/mL, respectively, was observed when treatment with lamivudine was added to treatment with adefovir dipivoxil.

13 NONCLINICAL TOXICOLOGY

13.1 Carcinogenesis, Mutagenesis, Impairment of Fertility

Long-term oral carcinogenicity studies of adefovir dipivoxil in mice and rats were carried out at exposures up to approximately 10 times (mice) and 4 times (rats) those observed in humans at the therapeutic dose for HBV infection. In both mouse and rat studies, adefovir dipivoxil was negative for carcinogenic findings. Adefovir dipivoxil was mutagenic in the in vitro mouse lymphoma cell assay (with or without metabolic activation). Adefovir induced chromosomal aberrations in the in vitro human peripheral blood lymphocyte assay without metabolic activation. Adefovir dipivoxil was not clastogenic in the in vivo mouse micronucleus assay and adefovir was not mutagenic in the Ames bacterial reverse mutation assay using S. typhimurium and E. coli strains in the presence or absence of metabolic activation. In reproductive toxicology studies, no evidence of impaired fertility was seen in male or female rats at systemic exposure approximately 19 times that achieved in humans at the therapeutic dose.

13.2 Animal Toxicology and/or Pharmacology

Toxicology Studies

Animal reproduction studies were conducted in rats and rabbits with orally administered adefovir dipivoxil and intravenously administered adefovir.

In rats and rabbits, no embryotoxicity or teratogenicity was shown from oral administration of adefovir dipivoxil at maternal doses producing systemic exposures approximately 23 times (rats) and 40 times (rabbits) that achieved in humans at the therapeutic dose of 10 mg/day.

When pregnant rats were administered intravenous adefovir at maternally toxic doses associated with systemic exposure 38 times that in humans, embryotoxicity and an increased incidence of fetal malformations (anasarca, depressed eye bulge, umbilical hernia, and kinked tail) were observed. No adverse effects on development were seen with intravenous adefovir administered to pregnant rats at a systemic exposure 12 times that in humans.

Animal Toxicology Studies

Renal tubular nephropathy characterized by histological alterations and/or increases in BUN and serum creatinine was the primary dose-limiting toxicity associated with administration of adefovir dipivoxil in animals. Nephrotoxicity was observed in animals at systemic exposures approximately 3–10 times higher than those in humans at the recommended therapeutic dose of 10 mg/day.

14 CLINICAL STUDIES

14.1 Studies 437 and 438 (Pivotal Studies)

HBeAg-Positive Chronic Hepatitis B

Study 437 was a randomized, double-blind, placebo-controlled, three-arm study in patients with HBeAg-positive chronic hepatitis B that allowed for a comparison between placebo and HEPSERA. The median age of patients was 33 years. Seventy-four percent were male, 59% were Asian, 36% were Caucasian, and 24% had prior interferon-α treatment. At baseline, patients had a median total Knodell Histology Activity Index (HAI) score of 10, a median serum HBV DNA level as measured by the Roche Amplicor Monitor polymerase chain reaction (PCR) assay (LLOQ = 1000 copies/mL) of 8.36 log10 copies/mL and a median ALT level of 2.3 times the upper limit of normal.

HBeAg-Negative (Anti-HBe Positive/HBV DNA Positive) Chronic Hepatitis B

Study 438 was a randomized, double-blind, placebo-controlled study in patients who were HBeAg-negative at screening, and anti-HBe positive. The median age of patients was 46 years. Eighty-three percent were male, 66% were Caucasian, 30% were Asian and 41% had prior interferon-α treatment. At baseline, the median total Knodell HAI score was 10, the median serum HBV DNA level as measured by the Roche Amplicor Monitor PCR assay (LLOQ = 1000 copies/mL) was 7.08 log10 copies/mL, and the median ALT was 2.3 times the upper limit of normal.

The primary efficacy endpoint in both studies was histological improvement at Week 48; results of which are shown in Table 4.

Table 4. Histological Response at Week 48 [Intent-to-Treat population (patients with ≥1 dose of study drug) with assessable baseline biopsies.]
 | Study 437 |  | Study 438
 | HEPSERA 10 mg (N=168) | Placebo (N=161) | HEPSERA 10 mg (N=121) | Placebo (N=57)
Improvement [Histological improvement defined as ≥2 point decrease in the Knodell necro-inflammatory score with no worsening of the Knodell fibrosis score.] | 53% | 25% | 64% | 35%
No Improvement | 37% | 67% | 29% | 63%
Missing/Unassessable Data | 10% | 7% | 7% | 2%

Table 5 illustrates the changes in Ishak Fibrosis Score by treatment group.

Table 5. Changes in Ishak Fibrosis Score at Week 48
 | Study 437 |  | Study 438
Number of Adequate Biopsy Pairs | HEPSERA 10 mg (N=152) | Placebo (N=149) | HEPSERA 10 mg (N=113) | Placebo (N=56)
Ishak Fibrosis Score Improved [Change of 1 point or more in Ishak Fibrosis Score.] | 34% | 19% | 34% | 14%
Unchanged | 55% | 60% | 62% | 50%
Worsened | 11% | 21% | 4% | 36%

At Week 48, improvement was seen with respect to mean change in serum HBV DNA (log10 copies/mL), normalization of ALT, and HBeAg seroconversion as compared to placebo in patients receiving HEPSERA (Table 6).

Table 6. Change in Serum HBV DNA, ALT Normalization, and HBeAg Seroconversion at Week 48
 | Study 437 |  | Study 438
 | HEPSERA 10 mg (N=171) | Placebo (N=167) | HEPSERA 10 mg (N=123) | Placebo (N=61)
Mean change ± SD in serum HBV DNA from baseline (log10 copies/mL) | –3.57 ± 1.64 | –0.98 ± 1.32 | –3.65 ± 1.14 | –1.32 ± 1.25
ALT normalization | 48% | 16% | 72% | 29%
HBeAg seroconversion | 12% | 6% | NA [Patients with HBeAg-negative disease cannot undergo HBeAg seroconversion.] | NA

Treatment Beyond 48 Weeks

In Study 437, continued treatment with HEPSERA to 72 weeks resulted in continued maintenance of mean reductions in serum HBV DNA observed at Week 48. An increase in the proportion of patients with ALT normalization was also observed in Study 437. The effect of continued treatment with HEPSERA on seroconversion is unknown.

In Study 438, patients who received HEPSERA during the first 48 weeks were re-randomized in a blinded manner to continue on HEPSERA or receive placebo for an additional 48 weeks. At Week 96, 50 of 70 (71%) of patients who continued treatment with HEPSERA had undetectable HBV DNA levels (<1000 copies/mL), and 47 of 64 (73%) of patients had ALT normalization. HBV DNA and ALT levels returned towards baseline in most patients who stopped treatment with HEPSERA.

From 141 eligible patients, there were 125 (89%) patients in Study 438 who chose to continue HEPSERA for up to 192 weeks or 240 weeks (4 years or 5 years). As these patients had already received HEPSERA for at least 48 weeks and appeared to be experiencing a benefit, they are not necessarily representative of patients initiating HEPSERA. Of these patients, 89/125 (71%) and 47/70 (67%) had an undetectable HBV DNA level (<1000 copies/mL) at Week 192 and Week 240, respectively. Of the patients who had an elevated ALT at baseline, 77/104 (74%) and 42/64 (66%) had a normal ALT at Week 192 and Week 240, respectively. Six (5%) patients experienced HBsAg loss.

14.2 Study 435 (Pre- and Post- Liver Transplantation Patients)

HEPSERA was also evaluated in an open-label, uncontrolled study of 467 chronic hepatitis B patients pre- (N=226) and post- (N=241) liver transplantation with clinical evidence of lamivudine- resistant hepatitis B virus (Study 435). At baseline, 60% of pre-liver transplantation patients were classified as Child-Pugh-Turcotte score of Class B or C. The median baseline HBV DNA as measured by the Roche Amplicor Monitor PCR assay (LLOQ = 1000 copies/mL) was 7.4 and 8.2 log10 copies/mL, and the median baseline ALT was 1.8 and 2.0 times the upper limit of normal in pre- and post-liver transplantation patients, respectively. Results of this study are displayed in Table 5. Treatment with HEPSERA resulted in a similar reduction in serum HBV DNA regardless of the patterns of lamivudine-resistant HBV DNA polymerase mutations at baseline. The significance of the efficacy results listed in Table 7 as they relate to clinical outcomes is not known.

Table 7. Efficacy in Pre- and Post-Liver Transplantation Patients at Week 48
Efficacy Parameter [Data are missing for 29% (HBV DNA) and 37% to 45% (CPT Score, Normalization of ALT, Albumin, Bilirubin, and PT) of total patients enrolled in the study.] | Pre-Liver Transplantation (N=226) | Post-Liver Transplantation (N=241)
Mean change ± SD in HBV DNA from baseline (log10 copies/mL) | –3.7 ± 1.6 (n=117) | –4.0 ± 1.6 (n=164)
Proportion with undetectable HBV DNA (< 1000 copies/mL) [Denominator is the number of patients with serum HBV DNA ≥1000 copies/mL at baseline using the Roche Amplicor Monitor PCR Assay (LLOQ = 1000 copies/mL) and non-missing value at Week 48.] | 77/109 (71%) | 64/159 (40%)
Stable or improved Child-Pugh-Turcotte score | 86/90 (96%) | 107/115 (93%)
Normalization of: [Denominator is patients with abnormal values at baseline and non-missing value at Week 48.]
ALT | 61/82 (74%) | 56/110 (51%)
Albumin | 43/54 (80%) | 21/26 (81%)
Bilirubin | 38/68 (58%) | 29/38 (76%)
Prothrombin time | 39/46 (85%) | 5/9 (56%)

14.3 Study 461 (Clinical Evidence of Lamivudine Resistance)

In Study 461, a double-blind, active controlled study in 59 chronic hepatitis B patients with clinical evidence of lamivudine-resistant hepatitis B virus, patients were randomized to receive either HEPSERA monotherapy or HEPSERA in combination with lamivudine 100 mg or lamivudine 100 mg alone. At Week 48, the mean ± SD decrease in serum HBV DNA as measured by the Roche Amplicor Monitor PCR assay (LLOQ = 1000 copies/mL) was 4.00 ± 1.41 log10 copies/mL for patients treated with HEPSERA and 3.46 ± 1.10 log10 copies/mL for patients treated with HEPSERA in combination with lamivudine. There was a mean decrease in serum HBV DNA of 0.31 ± 0.93 log10 copies/mL in patients receiving lamivudine alone. ALT normalized in 47% of patients treated with HEPSERA, in 53% of patients treated with HEPSERA in combination with lamivudine, and 5% of patients treated with lamivudine alone. The significance of these findings as they relate to clinical outcomes is not known.

14.4 Study 518 (Pediatric Study)

Study 518 was a double-blind, placebo-controlled, study in which 173 pediatric patients (ages 2 to <18 years) with chronic hepatitis B (CHB) infection and elevated ALT were randomized 2:1 (115 receiving adefovir dipivoxil and 58 receiving placebo). Randomization was stratified by prior treatment and age 2 to <7 years old (cohort 1), 7 to <12 years old (cohort 2), and 12 to <18 years old (cohort 3). All patients in cohort 3 received 10 mg tablet formulation; all patients in cohorts 1 and 2 received an investigational suspension formulation (0.3 mg/kg/day cohort 1, 0.25 mg/kg/day cohort 2) once daily. The primary efficacy endpoint was HBV DNA <1000 copies/mL plus normalization of ALT at the end of Week 48.

In cohort 3 (n=83), significantly more patients treated with HEPSERA achieved the primary efficacy endpoint at the end of 48 weeks of blinded treatment (23%) when compared to placebo-treated patients (0%). The proportion of patients from cohorts 1 and 2 who responded to treatment with adefovir dipivoxil was not statistically significant when compared to the placebo arm, although the adefovir plasma concentrations in these patients were comparable to those observed in older patients. Overall, 22 of 115 (19%) of pediatric patients who received adefovir dipivoxil vs. 1 of 58 (2%) of placebo treated patients responded to treatment by Week 48 [see Adverse Reactions (6.3), Use In Special Populations (8.4) and Clinical Pharmacology (12.3, 12.4)].

16 HOW SUPPLIED / STORAGE AND HANDLING

HEPSERA is available as tablets. Each tablet contains 10 mg of adefovir dipivoxil. The tablets are white and debossed with "10" and "GILEAD" on one side and the stylized figure of a liver on the other side. They are packaged as follows: Bottles of 30 tablets (NDC 61958-0501-1) containing desiccant (silica gel) and closed with a child-resistant closure.

STORAGE AND HANDLING

Store in original container at 25 °C (77 °F), excursions permitted to 15–30 °C (59–86 °F) (see USP Controlled Room Temperature).

Do not use if seal over bottle opening is broken or missing.

17 PATIENT COUNSELING INFORMATION

17.1 Instructions for Safe Use

See FDA-approved patient labeling

- Physicians should inform patients of the potential risks and benefits of HEPSERA and of alternative modes of therapy.
- Physicians should instruct their patients to
  - Read the Patient Package Insert before starting HEPSERA therapy.
  - Follow a regular dosing schedule to avoid missing doses.
  - Immediately report any severe abdominal pain, muscle pain, yellowing of the eyes, dark urine, pale stools, and/or loss in appetite.
  - Inform their doctor or pharmacist if they develop any unusual symptom(s), or if any known symptom persists or worsens.
- Patients should remain under the care of a physician when using HEPSERA.
- Patients should be advised that
  - The optimal duration of HEPSERA treatment and the relationship between treatment response and long-term outcomes such as hepatocellular carcinoma or decompensated cirrhosis are not known.
  - Patients should not discontinue Hepsera without first informing their physician [See Warnings and Precautions. (5.1)]
  - Routine laboratory monitoring and follow-up with a physician is important during HEPSERA therapy.
  - Obtaining HIV antibody testing prior to starting HEPSERA is important [See Warnings and Precautions. (5.3)]
  - HEPSERA should not be administered concurrently with VIREAD or TRUVADA or ATRIPLA [See Warnings and Precautions. (5.5)]
  - Lamivudine-resistant patients should use HEPSERA in combination with lamivudine and not as HEPSERA monotherapy [See Warnings and Precautions. (5.6)]

17.2 Pregnancy and Breastfeeding

- Physicians should inform women of childbearing age about the risks associated with exposure to HEPSERA during pregnancy.
- Patients should inform their physician if they become pregnant while using HEPSERA.
- Pregnant patients using HEPSERA should be informed about the HEPSERA pregnancy registry and offered the opportunity to enroll.
- Patients should be informed that it is not known whether HEPSERA is excreted into human milk or if it can harm a nursing infant. Therefore, a decision should be made whether to discontinue breastfeeding or drug.

Manufactured for: Gilead Sciences, Inc.
Foster City, CA 94404

HEPSERA® is a trademark of Gilead Sciences, Inc.
©2009 Gilead Sciences, Inc.

FDA-Approved Patient Labeling

PATIENT INFORMATION

HEPSERA® (hep-SER-rah)

Generic Name: (adefovir dipivoxil) tablets

Read this information carefully before you start taking HEPSERA. Read and check for new information each time you get more HEPSERA. This information does not take the place of talking with your doctor about your medical condition or your treatment.

What is the most important information I should know about HEPSERA?

1. Some people who stop taking HEPSERA get a very serious hepatitis. This usually happens within 12 weeks after stopping. You will need to have regular blood tests to check for liver function and hepatitis B virus levels if you stop taking HEPSERA.
2. HEPSERA may cause a severe kidney problem called nephrotoxicity. It usually happens in people that already have a kidney problem, but it can happen to anyone that uses HEPSERA. You will need to have regular blood tests to check for kidney function while you are taking HEPSERA.
3. If you get or have HIV that isn't being treated with medicines, HEPSERA may increase the chances your HIV infection cannot be helped with usual HIV medicines. This can happen if you get or have HIV and don't know it, or if your HIV is not being treated while you are taking HEPSERA. You should get an HIV test before you start taking HEPSERA and anytime after that when there's a chance you were exposed to HIV.
4. Some people who have taken medicines like HEPSERA that are called nucleoside or nucleotide analogs have developed a serious condition called lactic acidosis (build up of an acid in the blood). Lactic acidosis is a medical emergency and must be treated in the hospital. Call your doctor right away if you get any of the following signs of lactic acidosis:
  - You feel very weak or tired.
  - You have unusual (not normal) muscle pain.
  - You have trouble breathing.
  - You have stomach pain with nausea and vomiting.
  - You feel cold, especially in your arms and legs.
  - You feel dizzy or lightheaded.
  - You have a fast or irregular heartbeat.

Some people who have taken medicines like HEPSERA have developed serious liver problems called hepatotoxicity, with liver enlargement (hepatomegaly) and fat in the liver (steatosis). Call your doctor right away if you get any of the following signs of liver problems.

- Your skin or the white part of your eyes turns yellow (jaundice).
- Your urine turns dark.
- Your bowel movements (stools) turn light in color.
- You don't feel like eating food for several days or longer.
- You feel sick to your stomach (nausea).
- You have lower stomach pain.

You may be more likely to get lactic acidosis or serious liver problems if you are very overweight (obese) or have been taking nucleoside analog medicines [Atripla® (efavirenz plus emtricitabine plus tenofovir disoproxil fumarate), Combivir (zidovudine plus lamivudine), Emtriva® (emtricitabine), Epivir, Epivir-HBV (lamivudine), Epzicom (abacavir plus lamivudine), Hivid (zalcitabine), Retrovir (zidovudine), Trizivir (zidovudine plus lamivudine plus abacavir), Truvada® (emtricitabine plus tenofovir disoproxil fumarate), Videx (didanosine), Viread® (tenofovir disoproxil fumarate), Zerit (stavudine), and Ziagen (abacavir)] for a long time.

What is HEPSERA?

HEPSERA is a medicine used to treat patients at least 12 years of age with continuing (chronic) infections with active hepatitis B virus. HEPSERA has not been studied in adults over the age of 65 and is not recommended for use in children less than 12 years of age.

- HEPSERA will not cure your chronic hepatitis B.
- HEPSERA may help lower the amount of hepatitis B virus in your body.
- HEPSERA may lower the ability of the virus to multiply and infect new liver cells.
- We do not know if HEPSERA will reduce your chances of getting liver cancer or liver damage (cirrhosis) from chronic hepatitis B.
- We do not know how long HEPSERA may help your hepatitis. Sometimes viruses change in your body and medicines no longer work. This is called drug resistance.
- HEPSERA does not stop you from spreading hepatitis B virus to others by sex or sharing needles. So practice safe sex and needle use.

Who should not take HEPSERA?

- Do not take HEPSERA if you are allergic to any of the ingredients in HEPSERA. The active ingredient in HEPSERA is adefovir dipivoxil. See the end of this leaflet for a complete list of all the ingredients in HEPSERA.
- Do not take HEPSERA if you are already taking VIREAD, TRUVADA or ATRIPLA.

Tell your doctor if:

- You are pregnant. We do not know if HEPSERA can harm your unborn child. You and your doctor will need to decide if HEPSERA is right for you. If you take HEPSERA and you are pregnant, talk to your doctor about how you can join the HEPSERA pregnancy registry.
- You are breast-feeding. We do not know if HEPSERA can pass into your milk and if it can harm your baby. You will need to choose either to breast feed or take HEPSERA, but not both.
- You have kidney problems now or had them before. Your dose and schedule of HEPSERA may be reduced. Blood tests will need to be done regularly to see how your kidneys are working.

Tell your doctor about all the medicines you take, including prescription and non-prescription medicines, vitamins, and herbal supplements. Some medicines may affect how HEPSERA works, especially medicines that affect how your kidneys work. HEPSERA can affect how your other medicines work. Your dose of HEPSERA and the other medicines may be changed. Do not take any other medicines while you are taking HEPSERA, unless your doctor has told you it is okay.

How should I take HEPSERA?

- Your doctor will tell you how much HEPSERA to take.
- Your doctor will tell you when and how often to take HEPSERA.
- Take HEPSERA the same time each day that your doctor tells you. If you forget to take HEPSERA, take it as soon as you remember that day. Do not take more than 1 dose of HEPSERA in a day. Do not take 2 doses at the same time. Call your doctor or pharmacist if you are not sure what to do.
- Do not change your dose of HEPSERA or stop HEPSERA without talking to your doctor. Your hepatitis may get worse if you change doses or stop.
- You may take HEPSERA with or without food.
- When your HEPSERA supply gets low, call your doctor or pharmacy for a refill. Do not run out of HEPSERA.
- If you take too much HEPSERA, call your local poison control center or emergency room right away.

Some patients get worse or very serious hepatitis B symptoms when they stop taking HEPSERA (see, "What is the most important information I should know about HEPSERA?"). We don't know how long you should use HEPSERA. You and your doctor will need to decide when it is best for you to stop taking HEPSERA. After you stop taking HEPSERA, your doctor will still need to check your health and take blood tests to check your liver for a few months.

What should I avoid while taking HEPSERA?

Avoid doing things that can spread hepatitis B virus since HEPSERA doesn't stop you from passing the infection to others.

- Do not share needles or other injection equipment.
- Do not share personal items that can have blood or body fluids on them, like toothbrushes or razor blades.
- Do not have any kind of sex without protection. Practice "safe sex" using condoms and dental dams.

What are the possible side effects of HEPSERA?

HEPSERA can cause the following serious side effects: (see, "What is the most important information I should know about HEPSERA?")

1. a very serious hepatitis if you stop taking it.
2. a severe kidney problem called nephrotoxicity.
3. increase your chance of developing a form of HIV that cannot be treated with usual HIV medicines
4. lactic acidosis and liver problems.

The most common side effects of HEPSERA are weakness, headache, stomach pain, nausea, flatulence (intestinal gas), diarrhea, indigestion and changes in the way the kidneys work. Additional side effects in liver transplant patients with chronic hepatitis B are vomiting, rash and itching. Some patients with liver transplants also had undesirable effects on their kidneys, including failure of the kidneys.

Other side effects reported since HEPSERA has been marketed include kidney failure, damage to kidney cells, muscle pain or weakness and weakening of the bone, which could cause them to break (both associated with kidney problems), and inflammation of the pancreas.

These are not all of the possible side effects of HEPSERA. For more information, ask your doctor or pharmacist.

General information about the safe and effective use of HEPSERA:

Medicines are sometimes prescribed for conditions not mentioned in patient information leaflets. Do not use HEPSERA for a condition for which it was not prescribed. Do not give HEPSERA to other people, even if they have the same symptoms that you have.

This leaflet summarizes the most important information about HEPSERA. If you would like more information, talk with your doctor. You can ask your doctor or pharmacist for information about HEPSERA that is written for health professionals.

HEPSERA Tablets should be stored at room temperature and should be stored in their original container.

Do not use if seal over bottle opening is broken or missing.

What are the Ingredients of HEPSERA?

Active Ingredient: adefovir dipivoxil

Inactive Ingredients: croscarmellose sodium, lactose monohydrate, magnesium stearate, pregelatinized starch, and talc

Manufactured for: Gilead Sciences, Inc.
Foster City, CA 94404

VIREAD®, EMTRIVA®, and TRUVADA® are trademarks of Gilead Sciences, Inc. ATRIPLA® is a trademark of Bristol-Myers Squibb & Gilead Sciences, LLC. Other brands listed are the trademarks of their respective owners.

©2009 Gilead Sciences, Inc.

21-449-GS-011

PRINCIPAL DISPLAY PANEL - 30 CT Representative Label

HEPSERA® (ADEFOVIR DIPIVOXIL 10 MG)
TABLETS, 30 CT - BRITESTOCK

STORE BELOW 25°C

Part Number: 7000003

Lot Number: 1005247

Quantity: 080

CONTENTS MADE IN GERMANY
MANUFACTURED FOR:
GILEAD SCIENCES LIMITED
CORK, IRELAND

4000738.00